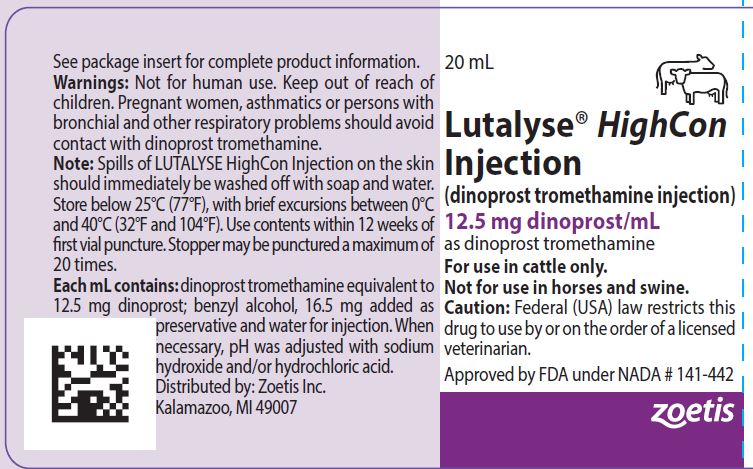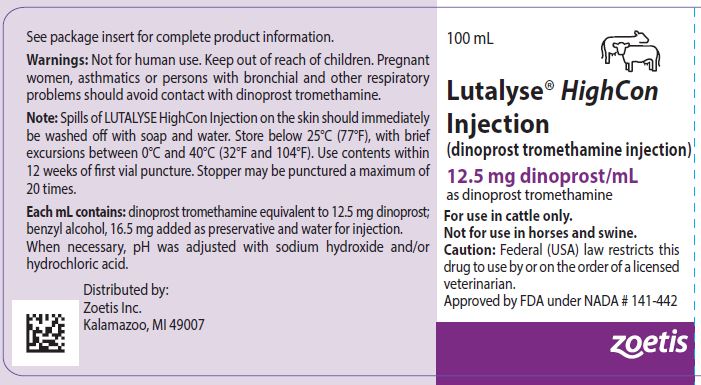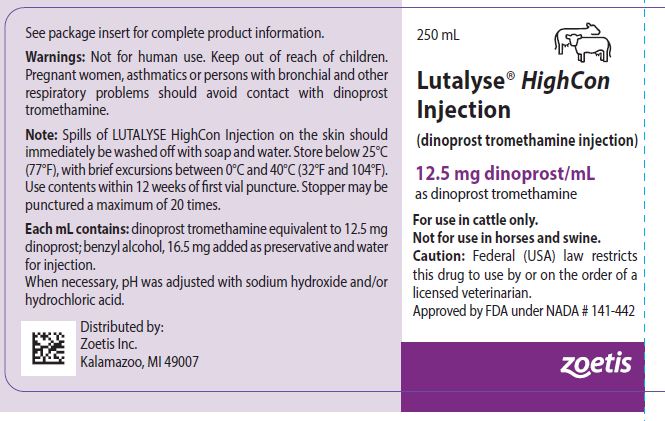 DRUG LABEL: Lutalyse HighCon
NDC: 54771-1328 | Form: INJECTION, SOLUTION
Manufacturer: Zoetis Inc.
Category: animal | Type: PRESCRIPTION ANIMAL DRUG LABEL
Date: 20240718

ACTIVE INGREDIENTS: DINOPROST TROMETHAMINE 12.5 mg/1 mL
INACTIVE INGREDIENTS: BENZYL ALCOHOL 16.5 mg/1 mL; SODIUM HYDROXIDE; HYDROCHLORIC ACID

Lutalyse® HighCon

Lutalyse® HighCon Injection
(dinoprost tromethamine injection)

12.5 mg dinoprost/mL as dinoprost tromethamine
For use in cattle only.
Not for use in horses and swine.

Caution: Federal (USA) law restricts this drug to use by or on the order of a licensed veterinarian.

DESCRIPTION

LUTALYSE® HighCon Injection (12.5 mg dinoprost/mL) is a sterile solution containing the naturally occurring prostaglandin F2 alpha (dinoprost) as the tromethamine salt. Each mL contains dinoprost tromethamine equivalent to 12.5 mg dinoprost: also, benzyl alcohol, 16.5 mg added as preservative and water for injection. When necessary, pH was adjusted with sodium hydroxide and/or hydrochloric acid. Dinoprost tromethamine is a white or slightly off-white crystalline powder that is readily soluble in water at room temperature in concentrations to at least 200 mg/mL.

INDICATIONS FOR USE

LUTALYSE HighCon Injection is indicated as a luteolytic agent. LUTALYSE HighCon Injection is effective only in those cattle having a corpus luteum, i.e., those which ovulated at least five days prior to treatment.
• For estrus synchronization in beef cows, beef heifers and replacement dairy heifers
• For unobserved (silent) estrus in lactating dairy cows with a corpus luteum
• For treatment of pyometra (chronic endometritis) in cattle
• For abortion in beef cows, beef heifers and replacement dairy heifers
• For use with FACTREL (gonadorelin injection) Injection to synchronize estrous cycles to allow fixed-time artificial insemination (FTAI) in lactating dairy cows
• For use with EAZI-BREED™ CIDR® (progesterone intravaginal insert) Cattle Insert for synchronization of estrus in lactating dairy cows
• For use with EAZI-BREED™ CIDR® (progesterone intravaginal insert) Cattle Insert for synchronization of estrus in suckled beef cows and replacement beef and dairy heifers, advancement of first postpartum estrus in suckled beef cows, and advancement of first pubertal estrus in beef heifers

MANAGEMENT CONSIDERATIONS

Many factors contribute to success and failure of reproduction management, and these factors are important also when time of breeding is to be regulated with LUTALYSE HighCon Injection. Some of these factors are:
a. Cattle must be ready to breed—they must have a corpus luteum and be healthy;
b. Nutritional status must be adequate as this has a direct effect on conception and the initiation of estrus in heifers or return of estrous cycles in cows following calving;
c. Physical facilities must be adequate to allow cattle handling without being detrimental to the animal;
d. Estrus must be detected accurately if timed Al is not employed;
e. Semen of high fertility must be used;
f. Semen must be inseminated properly.

A successful breeding program can employ LUTALYSE HighCon Injection effectively, but a poorly managed breeding program will continue to be poor when LUTALYSE HighCon Injection is employed unless other management deficiencies are remedied first. Cattle expressing estrus following LUTALYSE HighCon Injection are receptive to breeding by a bull. Using bulls to breed large numbers of cattle in heat following LUTALYSE HighCon Injection will require proper management of bulls and cattle. Future reproductive performance of animals that are not cycling will be unaffected by injection of LUTALYSE HighCon Injection.

DOSAGE AND ADMINISTRATION

As with any multi-dose vial, practice aseptic techniques in withdrawing each dose to decrease the possibility of post- injection bacterial infections. Adequately clean and disinfect the vial stopper prior to entry with a sterile needle and syringe. Use only sterile needles, and use each needle only once. No vial stopper should be entered more than 20 times.

1. For Estrus Synchronization in Beef Cows, Beef Heifers and Replacement Dairy Heifers. LUTALYSE HighCon Injection is used to control the timing of estrus and ovulation in estrous cycling cattle that have a corpus luteum. Inject a dose of 2 mL LUTALYSE HighCon Injection (25 mg dinoprost) intramuscularly or subcutaneously either once or twice at a 10 to 12 day interval. With the single injection, cattle should be bred at the usual time relative to estrus. With the two injections cattle can be bred after the second injection either at the usual time relative to detected estrus or at about 80 hours after the second injection of LUTALYSE HighCon Injection. Estrus is expected to occur 1 to 5 days after injection if a corpus luteum was present. Cattle that do not become pregnant to breeding at estrus on days 1 to 5 after injection will be expected to return to estrus in about 18 to 24 days.

2. For Unobserved (Silent) Estrus in Lactating Dairy Cows with a Corpus Luteum. Inject a dose of 2 mL LUTALYSE HighCon Injection (25 mg dinoprost) by intramuscular or subcutaneous injection. Breed cows as they are detected in estrus. If estrus has not been observed by 80 hours after injection, breed at 80 hours. If the cow returns to estrus, breed at the usual breed at the usual time relative to estrus.

3. For Treatment of Pyometra (chronic endometritis) in Cattle. Inject a dose of 2 mL LUTALYSE HighCon Injection (25 mg dinoprost) by intramuscular or subcutaneous injection.

4. For Abortion in Beef Cows, Beef Heifers and Replacement Dairy Heifers. LUTALYSE HighCon Injection is indicated for its abortifacient effect in beef cows, beef heifers and replacement dairy heifers during the first 100 days of gestation. Inject a dose of 2 mL LUTALYSE HighCon Injection (25 mg dinoprost) by intramuscular or subcutaneous injection. Cattle that abort will abort within 35 days of injection.

5. For use with FACTREL® (gonadorelin injection) Injection to synchronize estrous cycles to allow fixed-time artificial insemination (FTAI) in lactating dairy cows: Administer 2 to 4 mL FACTREL Injection (100-200 mcg gonadorelin) per cow as an intramuscular injection in a treatment regimen with the following framework:
• Administer the first dose of FACTREL Injection (2-4 mL) at Day 0
• Administer a dose of 2 mL LUTALYSE HighCon Injection (25 mg dinoprost) by intramuscular or subcutaneous injection 6-8 days after the first dose of FACTREL Injection.
• Administer a second dose of FACTREL Injection (2-4 mL) 30 to 72 hours after the LUTALYSE HighCon Injection.
• Perform FTAI 0 to 24 hours after the second dose of FACTREL Injection, or inseminate cows on detected estrus using standard herd practices.

Below are three examples of treatment regimens for the dosage regimen framework described immediately above:

 | Example 1 | Example 2 | Example 3
Day 0 (Monday) | 1st Factrel | 1st Factrel | 1st Factrel
Day 7 (the following Monday) | LUTALYSE; HighCon | LUTALYSE; HighCon | LUTALYSE; HighCon
Day 9 (Wednesday) | 2nd Factrel; + FTAI at 48 hours; after; LUTALYSE; HighCon | 2nd Factrel; at 48 hours; after; LUTALYSE; HighCon | 2nd Factrel; at 56 hours; after; LUTALYSE; HighCon
Day 10 (Thursday) |  | FTAI; 24 hours; after 2nd FACTREL | FTAI; 18 hours; after 2nd FACTREL

6. For use with EAZI-BREED™ CIDR® (progesterone intravaginal insert) Cattle Insert for Synchronization of Estrus in Lactating Dairy Cows:

• Administer one EAZI-BREED CIDR Cattle Insert per animal and remove 7 days later (for example if administered on a Monday remove the following Monday).
• Administer a dose of 2 mL LUTALYSE HighCon Injection (25 mg dinoprost) by intramuscular subcutaneous injection at the time of removal of the EAZI-BREED CIDR Cattle Insert.
• Observe animals for signs of estrus on Days 2 to 5 after removal of the EAZI-BREED CIDR Cattle Insert and inseminate animals found in estrus following normal herd practices.

7. For use with EAZI-BREED™ CIDR® (progesterone intravaginal insert) Cattle Insert for synchronization of estrus in suckled beef cows and replacement beef and dairy heifers, advancement of first postpartum estrus in suckled beef cows, and advancement of first pubertal estrus in beef heifers:

• Administer one EAZI-BREED CIDR Cattle Insert per animal for 7 days (for example, if administered on a Monday remove on the following Monday).
• Administer a dose of 2 mL LUTALYSE HighCon Injection (25 mg dinoprost) by intramuscular or subcutaneous injection 1 day prior to EAZI-BREED CIDR Cattle Insert removal, on Day 6 of the 7 day administration period.
• Observe animals for signs of estrus on Days 1 to 3 after removal of the EAZI-BREED CIDR Cattle Insert and inseminate animals about 12 hours after onset of estrus.

WARNINGS AND PRECAUTIONS

User Safety: Not for human use. Keep out of the reach of children. Women of childbearing age, asthmatics, and persons with bronchial and other respiratory problems should exercise extreme caution when handling this product. In the early stages, women may be unaware of their pregnancies. Dinoprost tromethamine is readily absorbed through the skin and can cause abortion and/or bronchiospasms. Accidental spillage on the skin should be washed off immediately with soap and water.
Residue Warnings: No milk discard or preslaughter drug withdrawal period is required for labeled uses in cattle. Use of this product in excess of the approved dose may result in drug residues.
Animal Safety Warnings: Severe localized clostridial infections associated with injection of LUTALYSE Injection have been reported. In rare instances, such infections have resulted in death. Aggressive antibiotic therapy should be employed at the first sign of infection at the injection site whether localized or diffuse. Do not administer intravenously (IV) as this route may potentiate adverse reactions. Nonsteroidal anti-inflammatory drugs may inhibit prostaglandin synthesis; therefore this class of drugs should not be administered concurrently. Do not administer to pregnant cattle, unless abortion is desired. Cattle administered a progestin would be expected to have a reduced response to LUTALYSE Injection.

ADVERSE REACTIONS

Limited salivation has been reported in some instances.

CONTACT INFORMATION

For a copy of the Safety Data Sheet or to report adverse reactions, call Zoetis Inc. at 1-888-963-8471. For additional information about adverse drug experience reporting for animal drugs, contact FDA at 1-888-FDA-VETS or www.fda.gov/reportanimalae.

CLINICAL PHARMACOLOGY

General Biologic Activity: Prostaglandins occur in nearly all mammalian tissues. Prostaglandins, especially PGE’s and PGF’s, have been shown, in certain species, to 1) increase at time of parturition in amniotic fluid, maternal placenta, myometrium, and blood, 2) stimulate myometrial activity, and 3) to induce either abortion or parturition. Prostaglandins, especially PGF2α, have been shown to 1) increase in the uterus and blood to levels similar to levels achieved by exogenous administration which elicited luteolysis, 2) be capable of crossing from the uterine vein to the ovarian artery (sheep), 3) be related to IUD induced luteal regression (sheep), and 4) be capable of regressing the corpus luteum of most mammalian species studied to date. Prostaglandins have been reported to result in release of pituitary tropic hormones. Data suggest prostaglandins, especially PGE’s and PGF’s, may be involved in the process of ovulation and gamete transport. Also PGF2α has been reported to cause increase in blood pressure, bronchoconstriction, and smooth muscle stimulation in certain species.

Metabolism: A number of metabolism studies have been done in laboratory animals. The metabolism of tritium labeled dinoprost (3H PGF2 alpha) in the rat and in the monkey was similar. Although quantitative differences were observed, qualitatively similar metabolites were produced. A study demonstrated that equimolar doses of 3H PGF2 alpha Tham and 3H PGF2 alpha free acid administered intravenously to rats demonstrated no significant differences in blood concentration of dinoprost. An interesting observation in the above study was that the radioactive dose of 3H PGF2 alpha rapidly distributed in tissues and dissipated in tissues with almost the same curve as it did in the serum. The half-life of dinoprost in bovine blood has been reported to be on the order of minutes. A complete study on the distribution of decline of 3H PGF2 alpha Tham in the tissue of rats was well correlated with thework done in the cow. Cattle serum collected during 24 hours after doses of 0 to 250 mg dinoprost have been assayed by RIA for dinoprost and the 15-keto metabolites. These data support previous reports that dinoprost has a half-life of minutes. Dinoprost is a natural prostaglandin. All systems associated with dinoprost metabolism exist in the body; therefore, no new metabolic, transport, excretory, binding or other systems need be established by the body to metabolize injected dinoprost.

Relative Bioavailability Study: The requirement for substantial evidence of effectiveness was fulfilled by a pharmacokinetic study comparing the relative bioavailability of the subcutaneous (SC) administration of 25 mg of LUTALYSE HighCon Injection (12.5 mg dinoprost/mL) to the approved intramuscular (IM) administration of 25 mg of LUTALYSE Injection (5 mg dinoprost/mL). The effectiveness data for LUTALYSE Injection at doses of 25 and 35 mg IM were used to support an adjusted Test/Reference (T/R) ratio of 1.4 and 90% Confidence Intervals of 80 - 164% for Cmax and AUC to demonstrate therapeutic equivalence.

The pivotal relative bioavailability study was a randomized, non-replicated, three treatment, three period, six sequence crossover study in 24 cows (4 cows per sequence). Each cow received a single dose of 25 mg dinoprost administered as 5 mL of LUTALYSE Injection IM, 5 mL of LUTALYSE Injection SC, or 2 mL of LUTALYSE HighCon SC, with a washout period of 48 hours between doses. Plasma samples were collected at 60 and 10 minutes prior to dose administration, and at 5, 10, 15, 20, 30, 75 minutes, and at 2, 3, 4.5, 6, 7.5, and 12 hours after each dose. Samples were analyzed by UPLC-MS/MS for PGF2α (dinoprost) and PGFm (metabolite) concentrations. PGFm was chosen as the analyte of interest because its concentrations are reflective of exogenously administered dinoprost (after subtraction of endogenous concentrations), and it has a longer half-life and therefore less blood level fluctuations than PGF2α. The results of the relative bioavailability study are summarized in Table 1. The Cmax and AUClast of LUTALYSE HighCon were within the adjusted 90% Confidence Intervals. Therefore, the SC administration of 25 mg of LUTALYSE HighCon was equivalent to the IM administration of 25 mg LUTALYSE Injection.

Table 1: Relative Bioavailability Results for LUTALYSE HighCon Injection

Parameter | Product/; Route | LSMean | Ratio; T/ R† | Lower; 90% CI | Upper; 90% CI
Cmax; (ng/mL) | LUTALYSE; Injection; (IM)* | 41.26
Cmax; (ng/mL) | LUTALYSE; Injection; (SC)* | 50.80 | 1.23 | 110.99 | 136.60
Cmax; (ng/mL) | LUTALYSE; HighCon; Injection; (SC) | 55.12 | 1.34 | 120.42 | 148.20
AUClast) (hr*ng/mL) | LUTALYSE; Injection; (IM)* | 66.85
AUClast) (hr*ng/mL) | LUTALYSE; Injection; (SC) | 67.25 | 1.00 | 96.26 | 105.12
AUClast) (hr*ng/mL) | LUTALYSE; HighCon Injection; (SC) | 65.81 | 0.98 | 94.20 | 102.87

Cmax - maximum plasma concentration

AUClast - the area under the plasma concentration vs. time curve from time of injection to the limit of quantification of the assay

* Reference product and route of administration

† Geometric means

TARGET ANIMAL SAFETY

Laboratory Animals: Dinoprost was non-teratogenic in rats when administered orally at 1.25, 3.2, 10.0 and 20.0 mg dinoprost/kg/day from day 6th-15th of gestation or when administered subcutaneously at 0.5 and 1.0 mg/kg/day on gestation days 6, 7 and 8 or 9, 10 and 11 or 12, 13 and 14. Dinoprost was non-teratogenic in the rabbit when administered either subcutaneously at doses of 0.5 and 1.0 mg dinoprost/kg/day on gestation days 6, 7 and 8 or 9, 10 and 11 or 12, 13 and 14 or 15, 16 and 17 or orally at doses of 0.01, 0.1 and 1.0 mg dinoprost/kg/day on days 6-18 or 5.0 mg/kg/day on days 8-18 of gestation. A slight and marked embryo lethal effect was observed in dams given 1.0 and 5.0 mg dinoprost/kg/day respectively. This was due to the expected luteolytic properties of the drug.

A 14-day continuous intravenous infusion study in rats at 20 mg PGF2α per kg body weight indicated prostaglandins of the F series could induce bone deposition. However, such bone changes were not observed in monkeys similarly administered 15 mg dinoprost per kg body weight for 14 days.

Cattle: In cattle, evaluation was made of clinical observations, clinical chemistry, hematology, urinalysis, organ weights, and gross plus microscopic measurements following treatment with various doses up to 250 mg dinoprost administered twice intramuscularly at a 10 day interval or doses of 25 mg administered daily for 10 days. There was no unequivocal effect of dinoprost on the hematology or clinical chemistry parameters measured. Clinically, a slight transitory increase in heart rate was detected. Rectal temperature was elevated about 1.5˚ F through the 6th hour after injection with 250 mg dinoprost, but had returned to baseline at 24 hours after injection. No dinoprost associated gross lesions were detected. There was no evidence of toxicological effects. Thus, dinoprost had a safety factor of at least 10X on injection (25 mg luteolytic dose vs. 250 mg safe dose), based on studies conducted with cattle. At luteolytic doses, dinoprost had no effect on progeny. If given to a pregnant cow, it may cause abortion; the dose required for abortion varies considerably with the stage of gestation. Induction of abortion in feedlot cattle at stages of gestation up to 100 days of gestation did not result in dystocia, retained placenta or death of heifers in the field studies. The smallness of the fetus at this early stage of gestation should not lead to complications at abortion. However, induction of parturition or abortion with any exogenous compound may precipitate dystocia, fetal death, retained placenta and/or metritis, especially at latter stages of gestation.

Injection Site Safety Summary: Eight non-lactating, non-pregnant dairy cows were injected with saline and eight animals were injected with LUTALYSE HighCon (12.5 mg dinoprost/mL @ 25 mg/animal) twice, at an interval of ten days. The first injection was administered in the left neck on Day 0 and the second injection was administered in the right neck on Day 10. Clinical observations were conducted on Days -14, -1, 0, 1, 2, 10, and 11, and injection site observations were conducted on all animals once on Days -14, -1, and once daily from Day 0 until Day 11. Animals were euthanized on Day 11. There were no abnormal clinical observations or general health observations related to drug administration during the conduct of the study. Injection site observations revealed no findings of erythema, heat, or sensitivity. No hardness was noted at the injection sites in any control animal post treatment administration. In the treated group, two animals had hardness noted on the right neck on Day 11. This hardness was probably a result of test article administration at that site on the previous day. No abnormal skin appearance was noted in any animal during this study. Swelling with a volume of 3.53 cm3 was observed on Day 11 in the right neck in one treated animal. At necropsy discoloration (variations of dark red, tan, gray, or yellow mottled) in the subcutaneous tissue was observed at all dinoprost injection sites. More discolored subcutaneous tissue was present at the Day 10 injection sites compared to the Day 0 injection sites. There was no discoloration observed in the deep muscle tissue. In summary, this study demonstrated that subcutaneous injection of LUTALYSE HighCon was well tolerated when injected subcutaneously into dairy cows at a dose of 25 mg dinoprost/cow twice at an interval of 10 days.

EFFECTIVENESS

The requirement for substantial evidence of effectiveness was fulfilled by a pharmacokinetic study comparing the relative bioavailability of the SC administration of 25 mg of LUTALYSE HighCon Injection (12.5 mg dinoprost/mL) to the approved IM administration of 25 mg of LUTALYSE Injection (5 mg dinoprost/ mL) (see CLINICAL PHARMACOLOGY, Relative Bioavailability Study). This study demonstrated the equivalence of the SC administration of 25 mg of LUTALYSE HighCon to the IM administration of 25 mg of LUTALYSE Injection. Therefore, the effectiveness studies conducted with LUTALYSE Injection support the effectiveness of LUTALYSE HighCon Injection.

For Treatment of Pyometra (chronic endometritis) in Cattle: In studies conducted with LUTALYSE Injection, pyometra was defined as presence of a corpus luteum in the ovary and uterine horns containing fluid but not a conceptus based on palpation per rectum. Return to normal was defined as evacuation of fluid and return of the uterine horn size to 40mm or less based on palpation per rectum at 14 and 28 days. Most cattle that recovered in response to LUTALYSE Injection recovered within 14 days after injection. After 14 days, recovery rate of treated cattle was no different than that of non-treated cattle.

For Abortion in Beef Cows, Beef Heifers and Replacement Dairy Heifers: Commercial cattle were palpated per rectum for pregnancy in six feedlots. The percent of pregnant cattle in each feedlot less than 100 days of gestation ranged between 26 and 84; 80% or more of the pregnant cattle were less than 150 days of gestation. The abortion rates following injection of LUTALYSE Injection increased with increasing doses up to about 25 mg. As examples, the abortion rates, over 7 feedlots on the dose titration study, were 22%, 50%, 71%, 90% and 78% for cattle up to 100 days of gestation when injected IM with LUTALYSE Injection doses of 0, 1 (5 mg), 2 (10 mg), 4 (20 mg) and 8 (40 mg) mL, respectively. The statistical predicted relative abortion rate based on the dose titration data was about 93% for the 5 mL (25 mg) LUTALYSE Injection dose for cattle injected up to 100 days of gestation.

For use with FACTREL® (gonadorelin injection) Injection to synchronize estrous cycles to allow fixed-time artificial insemination (FTAI) in lactating dairy cows: For a full description of the studies conducted for the use of FACTREL Injection and LUTALYSE Injection, please refer to the labeling for FACTREL Injection.

HOW SUPPLIED

LUTALYSE HighCon Injection is available in 20, 100 and 250 mL vials.

STORAGE, HANDLING AND DISPOSAL

Store below 25°C (77°F), with brief excursions between 0°C and 40°C (32°F and 104°F). Use contents within 12 weeks of first vial puncture. Stopper may be punctured a maximum of 20 times.

Approved by FDA under NADA # 141-442
zoetis
Distributed by:
Zoetis Inc.
Kalamazoo, MI 49007
Revised: September 2021
40034683